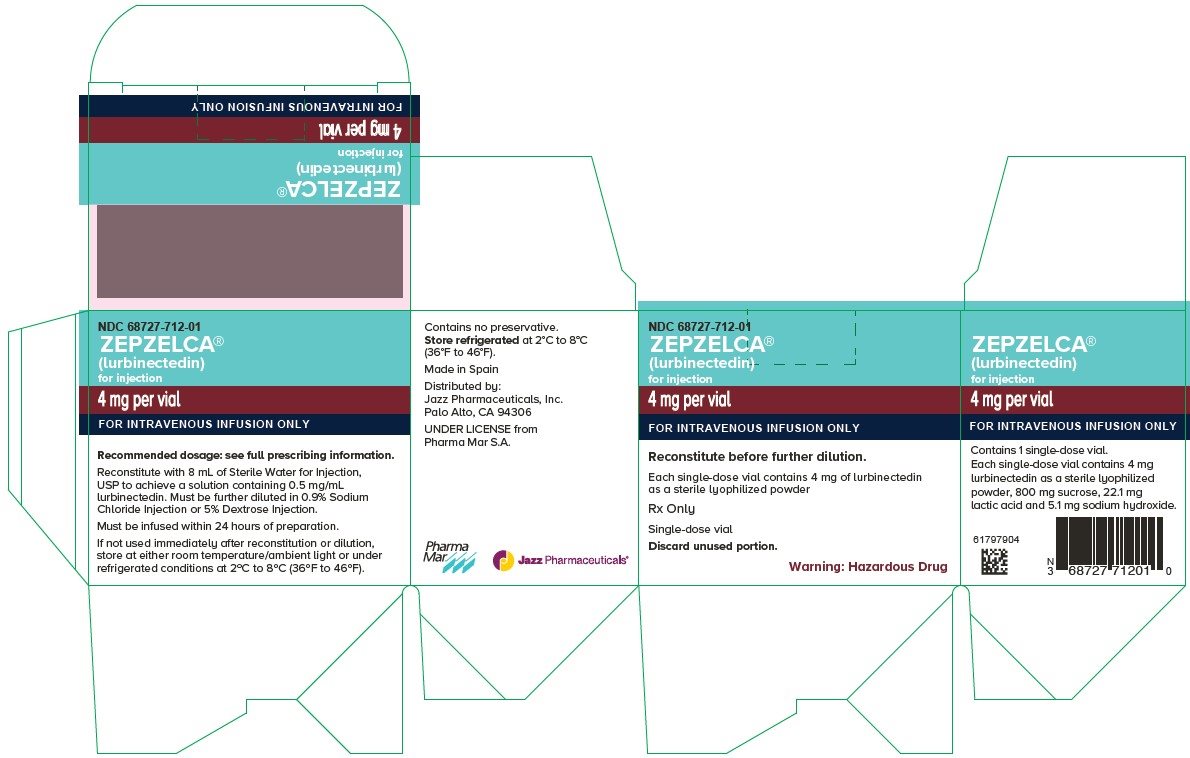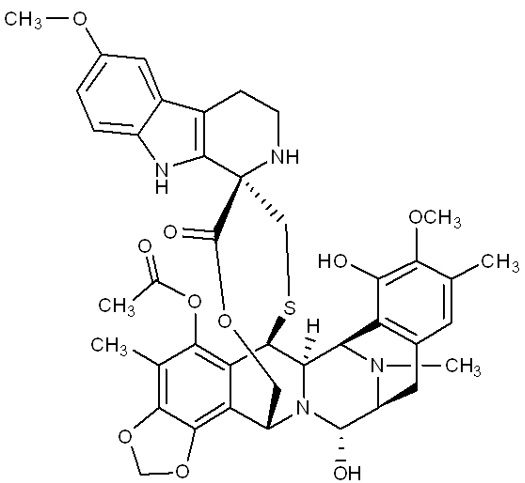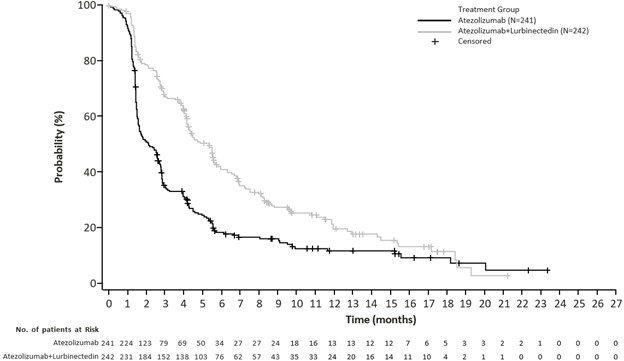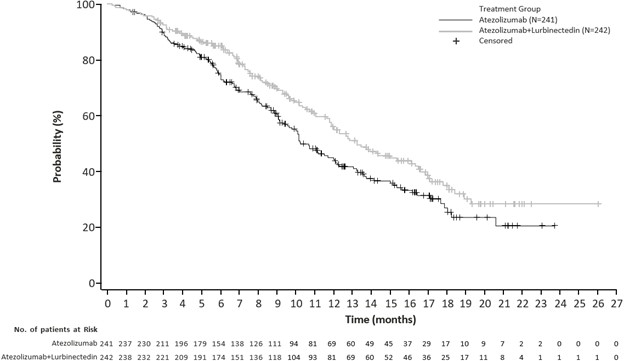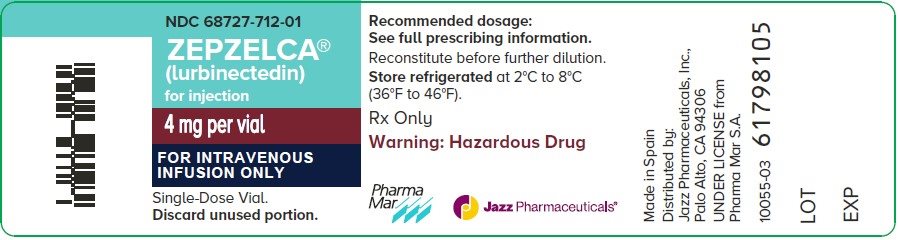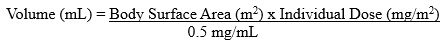 DRUG LABEL: ZEPZELCA
NDC: 68727-712 | Form: INJECTION, POWDER, LYOPHILIZED, FOR SOLUTION
Manufacturer: Jazz Pharmaceuticals, Inc.
Category: prescription | Type: HUMAN PRESCRIPTION DRUG LABEL
Date: 20251002

ACTIVE INGREDIENTS: LURBINECTEDIN .5 mg/1 mL
INACTIVE INGREDIENTS: SUCROSE 100 mg/1 mL; LACTIC ACID, UNSPECIFIED FORM 2.76 mg/1 mL; SODIUM HYDROXIDE .64 mg/1 mL; WATER 1 mL/1 mL

HIGHLIGHTS OF PRESCRIBING INFORMATION

These highlights do not include all the information needed to use ZEPZELCA safely and effectively. See full prescribing information for ZEPZELCA.
ZEPZELCA® (lurbinectedin) for injection, for intravenous use
Initial U.S. Approval: 2020

RECENT MAJOR CHANGES

Indications of Usage, Extensive-Stage Small Cell Lung Cancer (1.1) 10/2025

Dosage and Administration, Recommended Dosage (2.1) 10/2025

Dosage and Administration, Dosage Modifications for Use with Strong and Moderate CYP3A Inhibitors (2.3) 04/2025

Dosage and Administration, Dosage Modifications for Patients with Severe and Moderate Hepatic Impairment (2.4) 04/2025

Dosage and Administration, Premedication (2.5) 10/2025

Warnings and Precautions (5) 10/2025

1 INDICATIONS AND USAGE

ZEPZELCA is an alkylating drug indicated:

- in combination with atezolizumab or atezolizumab and hyaluronidase-tqj, for the maintenance treatment of adult patients with extensive-stage small cell lung cancer whose disease has not progressed after first-line induction therapy with atezolizumab or atezolizumab and hyaluronidase-tqjs, carboplatin and etoposide. (1.1)
- For the treatment of adult patients with metastatic small cell lung cancer (SCLC) with disease progression on or after platinum-based chemotherapy. (1.2)
This indication is approved under accelerated approval based on overall response rate and duration of response. Continued approval for this indication may be contingent upon verification and description of clinical benefit in a confirmatory trial(s). (1.2)

2 DOSAGE AND ADMINISTRATION

- Recommended Dosage: 3.2 mg/m^2 administered intravenously every 21 days until disease progression or unacceptable toxicity.
- Administration via a central venous line is recommended to reduce the risk of extravasation that can cause tissue necrosis requiring debridement. (5.3)
- Administer ZEPZELCA as an intravenous infusion over 60 minutes.
- To reduce the risk of nausea, administer corticosteroids and serotonin agonists prior to Cycle 1 and consider use for subsequent cycles. (2.5)
- To reduce the risk of febrile neutropenia during treatment with ZEPZELCA in combination with atezolizumab or atezolizumab and hyaluronidase-tqjs, administer granulocyte colony-stimulating factor (G-CSF) [Refer to Prescribing Information].
- Moderate Hepatic Impairment: Recommended dosage is 1.6 mg/m^2 administered intravenously every 21 days until disease progression or unacceptable toxicity. (2.4, 8.6)
- Severe Hepatic Impairment: Avoid use of ZEPZELCA. If use cannot be avoided, the recommended dosage is 1.6 mg/m^2 administered intravenously every 21 days until disease progression or unacceptable toxicity. (2.4, 8.6)

3 DOSAGE FORMS AND STRENGTHS

For injection: 4 mg lyophilized powder in a single-dose vial. (3)

4 CONTRAINDICATIONS

None. (4)

5 WARNINGS AND PRECAUTIONS

- Myelosuppression: Monitor blood counts prior to each administration. Initiate treatment with ZEPZELCA only if baseline neutrophil count is ≥ 1,500 cells/mm^3 and platelet count is ≥ 100,000/mm^3. For neutrophil count less than 500 cells/mm^3 or any value less than lower limit of normal, administer G-CSF. Withhold, reduce the dose, or permanently discontinue ZEPZELCA based on severity. (5.1)
- Hepatotoxicity: Monitor liver function tests prior to initiating ZEPZELCA, periodically during treatment and as clinically indicated. Withhold, reduce the dose, or permanently discontinue ZEPZELCA based on severity. (5.2)
- Extravasation Resulting in Tissue Necrosis: Consider use of a central venous catheter to reduce the risk of extravasation. Monitor patients for signs and symptoms of extravasation during the ZEPZELCA infusion. If extravasation occurs, immediately discontinue the infusion, remove the infusion catheter, and monitor for signs and symptoms of tissue necrosis. (5.3)
- Rhabdomyolysis: Monitor creatine phosphokinase (CPK) prior to initiating ZEPZELCA and periodically during treatment as clinically indicated. Withhold, reduce the dose, or permanently discontinue ZEPZELCA based on severity. (5.4)
- Embryo-Fetal Toxicity: Can cause fetal harm. Advise females and males of reproductive potential of the potential risk to a fetus and to use an effective method of contraception. (5.5)

6 ADVERSE REACTIONS

The most common adverse reactions for ZEPZELCA as a single agent, including laboratory abnormalities, (≥20%) are leukopenia, lymphopenia, fatigue, anemia, neutropenia, increased creatinine, increased alanine aminotransferase, increased glucose, thrombocytopenia, nausea, decreased appetite, musculoskeletal pain, decreased albumin, constipation, dyspnea, decreased sodium, increased aspartate aminotransferase, vomiting, cough, decreased magnesium and diarrhea. (6.1)

The most common adverse reactions, for ZEPZELCA in combination with atezolizumab including laboratory abnormalities, (≥ 30%) are: decreased lymphocytes, decreased platelets, decreased hemoglobin, decreased neutrophils, nausea, and fatigue/asthenia. (6.1)

To report SUSPECTED ADVERSE REACTIONS, contact Jazz Pharmaceuticals, Inc. at 1-800-520-5568 or FDA at 1-800-FDA-1088 or www.fda.gov/medwatch.

7 DRUG INTERACTIONS

Effect of Other Drugs on ZEPZELCA: Avoid coadministration with strong or a moderate CYP3A inhibitors and strong CYP3A inducers. (7.1)

8 USE IN SPECIFIC POPULATIONS

- Lactation: Advise not to breastfeed. (8.2)
- Hepatic Impairment: Avoid use of ZEPZELCA in patients with severe hepatic impairment. In patients with moderate hepatic impairment, reduce the dose of ZEPZELCA. (8.6)

FULL PRESCRIBING INFORMATION

1 INDICATIONS AND USAGE

1.1 Extensive-Stage Small Cell Lung Cancer

ZEPZELCA, in combination with atezolizumab or atezolizumab and hyaluronidase-tqjs, is indicated for the maintenance treatment of adult patients with extensive-stage small cell lung cancer (ES-SCLC) whose disease has not progressed after first-line induction therapy with atezolizumab or atezolizumab and hyaluronidase-tqjs, carboplatin and etoposide.

1.2 Metastatic Small Cell Lung Cancer

ZEPZELCA is indicated for the treatment of adult patients with metastatic small cell lung cancer (SCLC) with disease progression on or after platinum-based chemotherapy.

This indication is approved under accelerated approval based on overall response rate and duration of response [see Clinical Studies (14)]. Continued approval for this indication may be contingent upon verification and description of clinical benefit in a confirmatory trial(s).

2 DOSAGE AND ADMINISTRATION

2.1 Recommended Dosage

The recommended dosage of ZEPZELCA as a single-agent and as a combination with atezolizumab or atezolizumab and hyaluronidase-tqjs is 3.2 mg/m^2 by intravenous infusion over 60 minutes every 21 days until disease progression or unacceptable toxicity [see Dosage and Administration (2.4)].

Initiate treatment with ZEPZELCA only if absolute neutrophil count (ANC) is at least 1,500 cells/mm^3 and platelet count is at least 100,000/mm^3.

ZEPZELCA with Intravenous Atezolizumab or atezolizumab and hyaluronidase-tqjs

When administering ZEPZELCA on the same day as atezolizumab or atezolizumab and hyaluronidase-tqjs, administer the chosen atezolizumab drug first. For the recommended dosage of atezolizumab or atezolizumab and hyaluronidase-tqjs refer to the respective Prescribing Information.

If discontinuation of atezolizumab or atezolizumab and hyaluronidase-tqjs is required due to an immune-related severe adverse event, treatment with ZEPZELCA may be continued at the same dose as a single agent. If immune toxicity does not resolve or recurs despite discontinuation of atezolizumab, permanently discontinue ZEPZELCA.

2.2 Dosage Modifications for Adverse Reactions

The recommended dose reductions for adverse reactions are listed in Table 1.

Permanently discontinue ZEPZELCA in patients who require a dose interruption of greater than two weeks and in patients who are unable to tolerate 2 mg/m^2 every 21 days.

Table 1: Dose Reduction for ZEPZELCA for Adverse Reactions
Dose Reduction | Total Dose
First; Second | 2.6 mg/m^2 every 21 days; 2 mg/m^2 every 21 days

Dosage modifications for ZEPZELCA for adverse reactions are presented in Table 2.

Table 2: Dosage Modifications for ZEPZELCA for Adverse Reactions
Adverse Reaction | Severitya | Dosage Modification
Neutropeniab; [see Warnings and Precautions (5.1)] | Grade 4; or; Any grade febrile neutropenia | - Withhold ZEPZELCA until absolute neutrophil count (ANC) is ≥ 1500/mm^3 - Resume ZEPZELCA at a reduced dose
Thrombocytopenia; [see Warnings and Precautions (5.1)] | Grade 3 with bleeding; or; Grade 4 | - Withhold ZEPZELCA until platelet ≥ 100,000/mm^3 - Resume ZEPZELCA at reduced dose
Hepatotoxicity; [see Warnings and Precautions (5.2)] | Grade 2 | - Withhold ZEPZELCA until Grade ≤ 1 - Resume ZEPZELCA at same dose
Hepatotoxicity; [see Warnings and Precautions (5.2)] | Grade ≥ 3 | - Withhold ZEPZELCA until Grade ≤ 1 - Resume ZEPZELCA at reduced dose or permanently discontinue
Rhabdomyolysis; [see Warnings and Precautions (5.4)] | Grade 2 | - Withhold ZEPZELCA until Grade ≤ 1 - Resume ZEPZELCA at same dose
Rhabdomyolysis; [see Warnings and Precautions (5.4)] | Grade ≥ 3 | - Permanently discontinue ZEPZELCA.
Other Adverse Reactions; [see Adverse Reactions (6.1), Postmarketing (6.2)] | Grade 2 | - Withhold ZEPZELCA until Grade ≤ 1 - Resume ZEPZELCA at same dose
Other Adverse Reactions; [see Adverse Reactions (6.1), Postmarketing (6.2)] | Grade ≥ 3 | - Withhold ZEPZELCA until Grade ≤ 1 - Resume ZEPZELCA at reduced dose or permanently discontinue
a National Cancer Institute Common Terminology Criteria for Adverse Events (NCI CTCAE) version 4.0.
b Patients who have not received primary prophylaxis of G-CSF with isolated Grade 4 neutropenia (neutrophil count less than 500 cells/mm^3) may receive G-CSF prophylaxis rather than undergo lurbinectedin dose reduction.

2.3 Dosage Modifications for use with Strong and Moderate CYP3A Inhibitors

Avoid coadministration of ZEPZELCA with strong or moderate CYP3A inhibitors. If coadministration of ZEPZELCA with a strong or moderate CYP3A inhibitor cannot be avoided, reduce the dose of ZEPZELCA by 50% [see Drug Interactions (7.1) and Clinical Pharmacology (12.3)]. After discontinuation of a strong or moderate CYP3A inhibitor for 5 half-lives of the inhibitor, increase the ZEPZELCA dose to the dose used before starting the inhibitor.

2.4 Dosage Modifications for Patients with Severe and Moderate Hepatic Impairment

Avoid administration of ZEPZELCA in patients with severe hepatic impairment (total bilirubin > 3 × Upper Limit of Normal (ULN)). If administration of ZEPZELCA cannot be avoided, the recommended dosage is 1.6 mg/m^2 by intravenous infusion over 60 minutes every 21 days until disease progression or unacceptable toxicity [see Use in Specific Populations (8.6) and Clinical Pharmacology (12.3)].

In patients with moderate hepatic impairment (total bilirubin > 1.5 to ≤ 3 × ULN and any AST), the recommended dosage of ZEPZELCA is 1.6 mg/m^2 by intravenous infusion over 60 minutes every 21 days until disease progression or unacceptable toxicity.

2.5 Recommended Prophylactic Medications

ZEPZELCA as a Single-Agent

Consider administering the following pre-infusion medications for antiemetic prophylaxis [see Adverse Reactions (6.1)]:

- Corticosteroids (dexamethasone 8 mg intravenously or equivalent)
- Serotonin antagonists (ondansetron 8 mg intravenously or equivalent)

ZEPZELCA with Intravenous Atezolizumab or atezolizumab and hyaluronidase-tqjs

- To reduce the risk of febrile neutropenia during treatment with ZEPZELCA in combination with atezolizumab or atezolizumab and hyaluronidase-tqjs, administer granulocyte colony-stimulating factor (G-CSF) [Refer to Prescribing Information].
- To reduce the risk of nausea, administer the following pre-infusion medications for antiemetic prophylaxis prior to Cycle 1 and consider administering for subsequent cycles [see Adverse Reactions (6.1)]:
⸰ Corticosteroids (dexamethasone 8 mg or equivalent intravenously)
⸰ Serotonin antagonists (ondansetron 8 mg or equivalent intravenously)

2.6 Preparation, Administration and Storage

ZEPZELCA is a hazardous drug. Follow applicable special handling and disposal procedures^1.

Preparation

- Inject 8 mL of Sterile Water for Injection USP into the vial, yielding a solution containing 0.5 mg/mL lurbinectedin. Shake the vial until complete dissolution.
- Visually inspect the solution for particulate matter and discoloration. The reconstituted solution is a clear, colorless or slightly yellowish solution, free of visible particles.
- Calculate the required volume of reconstituted solution as follows:
- For administration through a central venous line, withdraw the appropriate amount of reconstituted solution from the vial and add to an infusion container containing at least 100 mL of diluent (0.9% Sodium Chloride Injection USP or 5% Dextrose Injection USP).
- For administration through a peripheral venous line, withdraw the appropriate amount of reconstituted solution from the vial and add to an infusion container containing at least 250 mL of diluent (0.9% Sodium Chloride Injection USP or 5% Dextrose Injection USP).

Administration

- Administration via a central venous line is recommended to reduce the risk of extravasation that can cause tissue necrosis requiring debridement [see Warnings and Precautions (5.3)].
- Parenteral drug products should be inspected visually for particulate matter and discoloration prior to administration, whenever solution and container permit. If particulate matter is observed, do not administer.
- ZEPZELCA can be administered with or without an in-line filter. If infusion lines containing in-line filters are utilized for administration of ZEPZELCA, polyethersulfone (PES) in-line filters with pore sizes of 0.22 micron are recommended.
  - Do not use in-line nylon membrane filters when the reconstituted ZEPZELCA solution is diluted using 0.9% Sodium Chloride Injection, USP. Adsorption of ZEPZELCA to the Nylon membrane filters has been observed when 0.9% Sodium Chloride Injection, USP is used as the diluent.

- Compatibility with other intravenous administration materials and the diluted ZEPZELCA solution has been demonstrated in the following materials:
  - Containers: Polyolefin containers (polyethylene, polypropylene and mixtures).
  - Infusion sets: Polyvinyl Chloride (PVC) (non-DEHP-containing), polyurethane and polyolefin infusion sets (polyethylene, polypropylene and polybutadiene).
  - Implantable venous access systems: Implantable venous access systems with titanium and plastic resin ports and with polyurethane or silicone intravenous catheters.
- Do not co-administer ZEPZELCA and other intravenous drugs concurrently within the same intravenous line.

ZEPZELCA with Intravenous Atezolizumab or atezolizumab and hyaluronidase-tqjs

- Administer either atezolizumab or atezolizumab and hyaluronidase-tqjs first, then administer ZEPZELCA. For the recommended dosage of atezolizumab or atezolizumab and hyaluronidase-tqjs refer to the respective Prescribing Information.

Storage of Infusion Solution

- If not used immediately after reconstitution or dilution, the ZEPZELCA solution can be stored prior to administration for up to 24 hours following reconstitution, including infusion time, at either room temperature/ ambient light or under refrigeration at 2ºC to 8ºC (36ºF to 46ºF) conditions.

3 DOSAGE FORMS AND STRENGTHS

For injection: 4 mg of lurbinectedin as a sterile, preservative-free, white to off-white lyophilized powder in a single-dose vial for reconstitution prior to intravenous infusion.

4 CONTRAINDICATIONS

None.

5 WARNINGS AND PRECAUTIONS

5.1 Myelosuppression

ZEPZELCA can cause severe and fatal myelosuppression including febrile neutropenia and sepsis, thrombocytopenia and anemia.

Administer ZEPZELCA only to patients with baseline neutrophil count of at least 1,500 cells/mm^3 and platelet count of at least 100,000/mm^3. To reduce the risk of febrile neutropenia during treatment with ZEPZELCA in combination with atezolizumab or atezolizumab and hyaluronidase-tqjs, administer granulocyte colony-stimulating factor (G-CSF) [refer to Prescribing Information].

Monitor blood counts including neutrophils, red blood cells and platelets prior to each ZEPZELCA administration. For neutrophil count less than 500 cells/mm^3 or any value less than lower limit of normal, administer G-CSF. Withhold, reduce the dose, or permanently discontinue ZEPZELCA based on severity [see Dosage and Administration (2.2)].

ZEPZELCA with Intravenous Atezolizumab

In the IMforte study [see Adverse Reactions (6.1)], primary prophylaxis of G-CSF was administered to 84% of patients. Based on laboratory values, decreased neutrophils occurred in 36%, including 18% Grade 3 or Grade 4 in patients who received ZEPZELCA in combination with atezolizumab. The median time to onset of Grade 3 and 4 decreased neutrophil cells was 31 days and a median duration of 10 days. Febrile neutropenia occurred in 1.7%. Sepsis occurred in 1%. There were 7 fatal infections: pneumonia (n=3), sepsis (n=3), and febrile neutropenia (n=1).

Based on laboratory values, decreased platelets occurred in 54%, including 15% Grade 3 or Grade 4 in patients who received ZEPZELCA in combination with atezolizumab. The median time to onset of Grade 3 and 4 decreased platelet cells was 31 days and a median duration of 12 days.

Based on laboratory values, decreased hemoglobin occurred in 51%, including 13% Grade 3 or Grade 4 in patients who received ZEPZELCA in combination with atezolizumab. The median time to onset of Grade 3 and 4 decreased hemoglobin was 64 days and a median duration of 8 days.

ZEPZELCA as a Single-Agent

In clinical studies of 554 patients with advanced solid tumors receiving ZEPZELCA as a single agent [see Adverse Reactions (6.1)], Grade 3 or 4 neutropenia occurred in 41% of patients, with a median time to onset of 15 days and a median duration of 7 days. Febrile neutropenia occurred in 7% of patients. Sepsis occurred in 2% of patients and was fatal in 1% (all cases occurred in patients with solid tumors other than SCLC). Grade 3 or 4 thrombocytopenia occurred in 10%, with a median time to onset of 10 days and a median duration of 7 days. Grade 3 or 4 anemia occurred in 17% of patients.

5.2 Hepatotoxicity

ZEPZELCA can cause hepatotoxicity which may be severe.

Monitor liver function tests prior to initiating ZEPZELCA and periodically during treatment as clinically indicated. Withhold, reduce the dose, or permanently discontinue ZEPZELCA based on severity [see Dosage and Administration (2.2)].

ZEPZELCA with Intravenous Atezolizumab

In the IMforte study [see Adverse Reactions (6.1)], based on laboratory values, increased alanine aminotransferase (ALT) occurred in 25%, including 3% Grade 3 or Grade 4 in patients who received ZEPZELCA in combination with atezolizumab. Increased aspartate aminotransferase (AST) occurred in 24% including 3% Grade 3 or Grade 4. The median time to onset of Grade ≥ 3 elevation in transaminases was 52 days (range: 6 to 337).

ZEPZELCA as a Single-Agent

In clinical studies of 554 patients with advanced solid tumors receiving ZEPZELCA as a single agent [see Adverse Reactions (6.1)], Grade 3 elevations of ALT and AST were observed in 6% and 3% of patients, respectively, and Grade 4 elevations of ALT and AST were observed in 0.4% and 0.5% of patients, respectively. The median time to onset of Grade ≥ 3 elevation in transaminases was 8 days (range: 3 to 49), with a median duration of 7 days.

5.3 Extravasation Resulting in Tissue Necrosis

Extravasation of ZEPZELCA can cause skin and soft tissue injury, including necrosis requiring debridement. Consider use of a central venous catheter to reduce the risk of extravasation, particularly in patients with limited venous access. Monitor patients for signs and symptoms of extravasation during the ZEPZELCA infusion. If extravasation occurs, immediately discontinue the infusion, remove the infusion catheter, and monitor for signs and symptoms of tissue necrosis. The time to onset of necrosis after extravasation may vary.

ZEPZELCA with Intravenous Atezolizumab

In the IMforte study [see Adverse Reactions (6.1)], extravasation resulting in skin necrosis occurred in one patient who received ZEPZELCA in combination with atezolizumab.

Administer supportive care and consult with an appropriate medical specialist as needed for signs and symptoms of extravasation. Administer subsequent infusions at a site that was not affected by extravasation.

5.4 Rhabdomyolysis

Rhabdomyolysis has been reported in patients treated with ZEPZELCA.

Monitor creatine phosphokinase (CPK) prior to initiating ZEPZELCA and periodically during treatment as clinically indicated. Withhold or reduce the dose based on severity [see Dosage and Administration (2.2)].

ZEPZELCA with Intravenous Atezolizumab

In the IMforte study [see Adverse Reactions (6.1)], among 235 patients who had a creatine phosphokinase laboratory evaluation, increased creatine phosphokinase occurred in 9% who received ZEPZELCA in combination with atezolizumab.

5.5 Embryo-Fetal Toxicity

Based on animal data and its mechanism of action ZEPZELCA can cause fetal harm when administered to a pregnant woman. Intravenous administration of a single dose of lurbinectedin (approximately 0.2 times the 3.2 mg/m^2 clinical dose) to pregnant animals during the period of organogenesis caused 100% embryolethality in rats. Advise pregnant women of the potential risk to a fetus. Advise female patients of reproductive potential to use effective contraception during treatment with ZEPZELCA and for 6 months after the last dose. Advise male patients with female partners of reproductive potential to use effective contraception during treatment with ZEPZELCA and for 4 months after the last dose [see Use in Specific Populations (8.1, 8.3)].

6 ADVERSE REACTIONS

The following clinically significant adverse reactions are described elsewhere in the labeling:

- Myelosuppression [see Warnings and Precautions (5.1)]
- Hepatotoxicity [see Warnings and Precautions (5.2)]
- Extravasation Resulting in Tissue Necrosis [see Warnings and Precautions (5.3)]
- Rhabdomyolysis [see Warnings and Precautions (5.4)]

6.1 Clinical Trials Experience

Because clinical trials are conducted under widely varying conditions, adverse reaction rates observed in the clinical trials of a drug cannot be directly compared to rates in the clinical trials of another drug and may not reflect the rates observed in practice.

The safety population described in the WARNINGS AND PRECAUTIONS reflects exposure to ZEPZELCA in combination with intravenous atezolizumab in the IMforte study [see Clinical Studies (14.1)], in 242 patients with extensive stage small cell lung cancer (ES-SCLC) whose disease had not progressed after initial therapy with atezolizumab, carboplatin, and etoposide. Patients received ZEPZELCA 3.2 mg/m^2 intravenously (IV) in combination with atezolizumab 1200 mg IV every 21 days until disease progression or unacceptable toxicity. Among 242 patients who received ZEPZELCA in combination with intravenous atezolizumab, 34% were exposed for 6 months or longer and 8% were exposed for greater than one year. The most common adverse reactions (≥ 30%), including laboratory abnormalities, in patients who received ZEPZELCA with atezolizumab were decreased lymphocytes, decreased platelets, decreased hemoglobin, decreased neutrophils, nausea, and fatigue/asthenia.

The pooled safety population described in the WARNINGS AND PRECAUTIONS also reflects exposure to ZEPZELCA as a single agent at a dose of 3.2 mg/m^2 intravenously every 21 days in 554 patients with advanced solid tumors. Among 554 patients who received ZEPZELCA, including 105 patients with small cell lung cancer (SCLC) in PM1183-B-005-14 (Study B-005), 24% were exposed for 6 months or longer and 5% were exposed for greater than one year. The most common adverse reactions for ZEPZELCA as a single agent, (Study B-005), including laboratory abnormalities, (≥ 20%) are leukopenia, lymphopenia, fatigue, anemia, neutropenia, increased creatinine, increased alanine aminotransferase, increased glucose, thrombocytopenia, nausea, decreased appetite, musculoskeletal pain, decreased albumin, constipation, dyspnea, decreased sodium, increased aspartate aminotransferase, vomiting, cough, decreased magnesium and diarrhea.

Extensive-Stage Small Cell Lung Cancer (IMforte)

The safety of ZEPZELCA in combination with intravenous (IV) atezolizumab was evaluated in IMforte [see Clinical Studies (14)]. Patients received intravenous ZEPZELCA 3.2 mg/m^2 in combination with intravenous atezolizumab 1200 mg on Day 1 of each 21-day cycle until disease progression or unacceptable toxicity. Primary prophylaxis of G-CSF was administered to 84% of patients. Among 242 patients who received ZEPZELCA with atezolizumab, the median duration of exposure to lurbinectedin was 4.1 months, 33% were exposed for 6 months or longer and 8% were exposed for greater than one year.

The median age of patients who received ZEPZELCA in combination with intravenous atezolizumab was 66 years (range: 35 to 85); 62% male; 82% White, 13% Asian, and 0.8% Black or African American.

Serious adverse reactions occurred in 31% of patients receiving ZEPZELCA in combination with atezolizumab. Serious adverse reactions occurring in > 2% were pneumonia (2.5%), respiratory tract infection (2.1%), dyspnea (2.1%), and decreased platelet count (2.1%). Fatal adverse reactions occurred in 5% of patients receiving ZEPZELCA with atezolizumab including pneumonia (3 patients), sepsis (3 patients), cardio-respiratory arrest (2 patients), myocardial infarction (2 patients), and febrile neutropenia (1 patient).

Permanent discontinuation of ZEPZELCA due to an adverse reaction occurred in 5% of patients. The adverse reaction resulting in permanent discontinuation in ≥ 1% of patients who received ZEPZELCA was decreased neutrophil count.

Dosage interruptions of ZEPZELCA due to an adverse reaction occurred in 25%. Adverse reactions which required dosage interruption in ≥ 2% of patients included anemia, fatigue, decreased neutrophil count, and decreased platelet count.

Dose reductions of ZEPZELCA due to an adverse reaction occurred in 15% of patients. Adverse reactions which required dosage reduction in ≥ 2% of patients included decreased platelet count, fatigue, nausea and vomiting.

Tables 3 summarizes the adverse reactions in IMforte.

Table 3: Adverse Reactions (≥ 10%) in Patients with ES-SCLC Who Received ZEPZELCA in Combination with Intravenous Atezolizumab in IMforte
Adverse Reaction | ZEPZELCA with Atezolizumab N = 242 |  | Atezolizumab N = 240
Adverse Reaction | All Grades (%) | Grade 3 or 4 (%) | All Grades (%) | Grade 3 or 4 (%)
Gastrointestinal
Nausea | 36 | 3 | 4 | 1
Diarrhea^1 | 15 | 0 | 8 | 0
Vomiting | 14 | 1 | 3 | 0
Constipation | 12 | 0 | 6 | 1
General disorders and administration site conditions
Fatigue^2 | 32 | 5 | 13 | 2
Musculoskeletal and connective tissue disorders
Musculoskeletal Pain^3 | 19 | 2 | 16 | 1
Metabolism and Nutrition
Decreased appetite | 17 | 0 | 7 | 0
Respiratory, thoracic and mediastinal disorders
Cough^4 | 12 | 0 | 8 | 0
Dyspnea^5 | 11 | 2 | 10 | 2
Graded per NCI CTCAE v5.0
^1 Includes diarrhea and colitis
^2 Includes fatigue and asthenia.
^3 Includes arthralgia, arthritis, back pain, bone pain, musculoskeletal chest pain, musculoskeletal discomfort, musculoskeletal pain, myalgia, neck pain, non-cardiac chest pain, and pain in extremity.
^4 Includes cough, productive cough, and upper-airway cough syndrome.
^5 Includes dyspnea and dyspnea exertional.

Clinically relevant adverse reactions in < 10% of patients who received ZEPZELCA in combination with intravenous atezolizumab included pneumonia, phlebitis, extravasation resulting in skin necrosis, hypersensitivity, and increased creatine phosphokinase.

Table 4 summarizes the laboratory abnormalities in IMforte.

Table 4: Select Laboratory Abnormalities (≥ 20%) That Worsened from Baseline in Patients with ES‑SCLC Who Received ZEPZELCA in Combination with Intravenous Atezolizumab in IMforte
Laboratory Abnormality | ZEPZELCA with Atezolizumab N = 242 |  | Atezolizumab N = 240
Laboratory Abnormality | All Grades (%) | Grade 3 or 4 (%) | All Grades (%) | Grade 3 or 4 (%)
Hematology
Decreased lymphocytes | 55 | 17 | 31 | 11
Decreased platelets | 54 | 15 | 15 | 3
Decreased hemoglobin | 51 | 13 | 12 | 3
Decreased neutrophils | 36 | 18 | 7 | 4
Chemistry
Increased alkaline phosphatase | 29 | 1 | 14 | 0
Decreased sodium | 27 | 4 | 30 | 5
Increased ALT | 25 | 3 | 18 | 2
Increased AST | 24 | 3 | 22 | 1
Decreased calcium | 24 | 3 | 8 | 1
Increased creatinine | 21 | 3 | 14 | 0
Graded per NCI CTCAE v5.0

Metastatic Small Cell Lung Cancer (SCLC) (Study B-005)

The safety of ZEPZELCA was evaluated in a cohort of 105 patients with previously treated SCLC in Study B-005 [see Clinical Studies (14)]. Patients received ZEPZELCA 3.2 mg/m^2 intravenously every 21 days. All patients in this study received a pre-specified anti-emetic regimen consisting of a corticosteroid and serotonin antagonist. Patients could receive G-CSF for secondary prophylaxis (i.e., after patients had an initial decrease in WBC), but not primary prophylaxis. Among patients who received ZEPZELCA, 29% were exposed for 6 months or longer and 6% were exposed for greater than one year.

Serious adverse reactions occurred in 34% of patients who received ZEPZELCA. Serious adverse reactions in ≥ 3% of patients included pneumonia, febrile neutropenia, neutropenia, respiratory tract infection, anemia, dyspnea, and thrombocytopenia.

Permanent discontinuation due to an adverse reaction occurred in two patients (1.9%) who received ZEPZELCA. Adverse reactions resulting in permanent discontinuation in ≥ 1% of patients who received ZEPZELCA, which included peripheral neuropathy and myelosuppression.

Dosage interruptions due to an adverse reaction occurred in 30.5% of patients who received ZEPZELCA. Adverse reactions requiring dosage interruption in ≥ 3% of patients who received ZEPZELCA included neutropenia, and hypoalbuminemia.

Dose reductions due to an adverse reaction occurred in 25% of patients who received ZEPZELCA. Adverse reactions requiring dosage reductions in ≥ 3% of patients who received ZEPZELCA included neutropenia, febrile neutropenia and fatigue.

The most common adverse reactions, including laboratory abnormalities, (≥ 20%) were leukopenia, lymphopenia, fatigue, anemia, neutropenia, increased creatinine, increased alanine aminotransferase, increased glucose, thrombocytopenia, nausea, decreased appetite, musculoskeletal pain, decreased albumin, constipation, dyspnea, decreased sodium, increased aspartate aminotransferase, vomiting, cough, decreased magnesium and diarrhea.

Table 5 summarizes the adverse reactions in the SCLC cohort of Study B-005.

Table 5: Adverse Reactions (≥ 10%) in Patients with SCLC Who Received ZEPZELCA in Study B-005
Adverse Reaction | ZEPZELCA (n=105)
Adverse Reaction | All Gradesa,b (%) | Grades 3-4 (%)
General disorders
Fatigue | 77 | 12
Pyrexia | 13 | 0
Chest pain | 10 | 0
Gastrointestinal disorders
Nausea | 37 | 0
Constipation | 31 | 0
Vomiting | 22 | 0
Diarrhea | 20 | 4
Abdominal painc | 11 | 1
Musculoskeletal and connective tissue disorders
Musculoskeletal paind | 33 | 4
Metabolism and nutrition disorders
Decreased appetite | 33 | 1
Respiratory, thoracic and mediastinal disorders
Dyspnea | 31 | 6
Coughe | 20 | 0
Infections and infestations
Respiratory tract infectionf | 18 | 5
Pneumoniag | 10 | 7
Nervous system disorders
Peripheral neuropathyh | 11 | 1
Headache | 10 | 1
a Graded per NCI CTCAE 4.0.
b No grade 5 adverse reactions were reported.
c Includes abdominal pain, abdominal pain upper and abdominal discomfort.
d Includes musculoskeletal pain, back pain, arthralgia, pain in extremity, musculoskeletal chest pain, neck pain, bone pain and myalgia.
e Includes cough and productive cough.
f Includes upper respiratory tract infection, viral upper respiratory tract infection, respiratory tract infection and bronchitis.
g Includes pneumonia and lung infection.
h Includes neuropathy peripheral, neuralgia, paresthesia, peripheral sensory neuropathy, hypoesthesia, and hyperesthesia.

Clinically relevant adverse reactions in < 10% of patients who received ZEPZELCA include dysgeusia, febrile neutropenia and pneumonitis.

Table 6 summarizes the laboratory abnormalities in Study B-005.

Table 6: Select Laboratory Abnormalities (≥ 20%) Worsening from Baseline in Patients with SCLC Who Received ZEPZELCA in Study B-005
Laboratory Abnormality | ZEPZELCAa (n=105)
Laboratory Abnormality | All Gradesb (%) | Grades 3-4 (%)
Hematology
Decreased leukocytes | 79 | 29
Decreased lymphocytes | 79 | 43
Decreased hemoglobin | 74 | 10
Decreased neutrophils | 71 | 46
Decreased platelets | 37 | 7
Chemistry
Increased creatinine | 69 | 0
Increased alanine aminotransferase | 66 | 4
Increased glucose | 52 | 5
Decreased albumin | 32 | 1
Decreased sodium | 31 | 7
Increased aspartate aminotransferase | 26 | 2
Decreased magnesium | 22 | 0
a The denominator used to calculate the rate varied from 95 to 105 based on the number of patients with a baseline value and at least one post-treatment value.
b Graded per NCI CTCAE 4.0.

6.2 Postmarketing Experience

The following adverse reactions have been identified during post-approval use of ZEPZELCA. Because these reactions are reported voluntarily from a population of uncertain size, it is not always possible to reliably estimate their frequency or establish a causal relationship to drug exposure.

General disorders and administration site conditions: Extravasation including tissue necrosis requiring debridement.

Musculoskeletal and Connective Tissue Disorders: Rhabdomyolysis.

Metabolism and nutrition disorders: Tumor lysis syndrome.

7 DRUG INTERACTIONS

7.1 Effect of Other Drugs on ZEPZELCA

Strong and Moderate CYP3A Inhibitors

Coadministration of ZEPZELCA with a strong or a moderate CYP3A inhibitor increases lurbinectedin systemic exposure [see Clinical Pharmacology (12.3)], which may increase the incidence and severity of adverse reactions to ZEPZELCA.

Avoid grapefruit and Seville oranges during ZEPZELCA treatment, as these contain strong or moderate inhibitors of CYP3A.

Avoid coadministration of ZEPZELCA with strong or moderate CYP3A inhibitors. If coadministration cannot be avoided, reduce the dose of ZEPZELCA [see Dosage and Administration (2.3)].

Strong CYP3A Inducers

Avoid coadministration of ZEPZELCA with strong CYP3A inducers. Coadministration of ZEPZELCA with a strong CYP3A inducer may decrease lurbinectedin systemic exposure, which may decrease the efficacy of ZEPZELCA [see Clinical Pharmacology (12.3)].

8 USE IN SPECIFIC POPULATIONS

8.1 Pregnancy

Risk Summary

Based on animal data and its mechanism of action [see Clinical Pharmacology (12.1)], ZEPZELCA can cause fetal harm when administered to a pregnant woman. There are no available data to inform the risk of ZEPZELCA use in pregnant women. Intravenous administration of a single lurbinectedin dose (approximately 0.2 times the 3.2 mg/m^2 clinical dose) to pregnant rats during the period of organogenesis caused embryolethality (see Data).

Advise pregnant women of the potential risk to a fetus.

The estimated background risk of major birth defects and miscarriage for the indicated population is unknown. All pregnancies have a background risk of birth defect, loss, or other adverse outcomes. In the U.S. general population, the estimated background risk of major birth defects and miscarriage in clinically recognized pregnancies is 2 to 4% and 15 to 20%, respectively.

Data

Animal Data

In a reproductive toxicity study, administration of a single lurbinectedin dose of 0.6 mg/m^2 (approximately 0.2 times of the human dose of 3.2 mg/m^2) to pregnant rats on Gestation Day 10 resulted in 100% post-implantation loss.

8.2 Lactation

Risk Summary

There are no data on the presence of lurbinectedin in human milk or its effects on the breastfed child or on milk production. Because of the potential for serious adverse reactions from ZEPZELCA in breastfed children, advise women not to breastfeed during treatment with ZEPZELCA and for 2 weeks after the last dose.

8.3 Females and Males of Reproductive Potential

ZEPZELCA can cause embryolethality at doses lower than the human dose of 3.2 mg/m^2 [see Use in Specific Populations (8.1)].

Pregnancy Testing

Verify the pregnancy status of females of reproductive potential prior to initiating ZEPZELCA.

Contraception

Females

Advise female patients of reproductive potential to use effective contraception during treatment with ZEPZELCA and for 6 months after the last dose.

Males

Advise males with a female sexual partner of reproductive potential to use effective contraception during treatment with ZEPZELCA and for 4 months after the last dose.

8.4 Pediatric Use

The safety and effectiveness of ZEPZELCA in pediatric patients have not been established.

8.5 Geriatric Use

ZEPZELCA with Intravenous Atezolizumab

Of the 242 patients with ES-SCLC treated with ZEPZELCA and atezolizumab in IMforte, 124 (51%) patients were 65 years of age and older, while 29 (12%) patients were 75 years of age and older. No overall differences in effectiveness were observed between older and younger patients. There was no overall difference in the incidence of serious adverse reactions in patients ≥ 65 years of age and patients < 65 years of age (33% vs. 29%, respectively). There was a higher incidence of Grade 3 or 4 adverse reactions in patients ≥ 65 years of age compared to younger patients (45% vs. 31%, respectively).

ZEPZELCA as a single agent

Of the 105 patients with SCLC administered ZEPZELCA in clinical studies, 37 (35%) patients were 65 years of age and older, while 9 (9%) patients were 75 years of age and older. No overall difference in effectiveness was observed between patients aged 65 and older and younger patients.

There was a higher incidence of serious adverse reactions in patients ≥ 65 years of age than in patients < 65 years of age (49% vs. 26%, respectively). The serious adverse reactions most frequently reported in patients ≥ 65 years of age were related to myelosuppression and consisted of febrile neutropenia (11%), neutropenia (11%), thrombocytopenia (8%), and anemia (8%) [see Adverse Reactions (6.1)]. There was a higher incidence of Grade 3 or 4 adverse reactions in patients ≥ 65 years of age compared to younger patients (76% vs. 50%, respectively).

8.6 Hepatic Impairment

Avoid administration of ZEPZELCA in patients with severe hepatic impairment (total bilirubin > 3 × ULN). If administration of ZEPZELCA cannot be avoided, reduce the dose [see Dosage and Administration (2.4)]. Monitor for increased adverse reactions in patients with severe hepatic impairment.

Reduce the dose of ZEPZELCA in patients with moderate hepatic impairment (total bilirubin > 1.5 to 3 × ULN and any AST) [see Dosage and Administration (2.4)]. Monitor for increased adverse reactions in patients with moderate hepatic impairment.

No dose adjustment of ZEPZELCA is recommended for patients with mild hepatic impairment (total bilirubin ≤ ULN and AST > ULN, or total bilirubin 1 to ≤ 1.5 × ULN and any AST) [see Clinical Pharmacology (12.3)].

11 DESCRIPTION

ZEPZELCA is an alkylating drug. The chemical name of ZEPZELCA (lurbinectedin) is (1’R,6R,6aR,7R,13S,14S,16R)-8,14-dihydroxy-6’,9-dimethoxy-4,10,23-trimethyl-19-oxo-2’,3’,4’,6,7,9’,12,13,14,16-decahydro-6aH-spiro[7,13-azano-6,16-(epithiopropanooxymethano) [1,3]dioxolo[7,8]isoquinolino[3,2-b][3]benzazocine-20,1’-pyrido[3,4-b]indol]-5-yl acetate.

The molecular formula is C41H44N4O10S. The molecular weight is 784.87g/mol, and the chemical structure is:

ZEPZELCA for injection 4 mg is supplied as a lyophilized powder in a single-dose vial for reconstitution for intravenous use. The ZEPZELCA lyophilized formulation is comprised of 4 mg lurbinectedin, sucrose (800 mg), lactic acid (22.1 mg), and sodium hydroxide (5.1 mg). Before use, the lyophilizate is reconstituted by addition of 8 mL Sterile Water for Injection USP, yielding a solution containing 0.5 mg/mL lurbinectedin (the calculated concentration is 0.47 mg/mL based on the final volume of 8.5 mL).

12 CLINICAL PHARMACOLOGY

12.1 Mechanism of Action

Lurbinectedin is an alkylating drug that binds guanine residues in the minor groove of DNA, forming adducts and resulting in a bending of the DNA helix towards the major groove. Adduct formation triggers a cascade of events that can affect the subsequent activity of DNA binding proteins, including some transcription factors, and DNA repair pathways, resulting in perturbation of the cell cycle and eventual cell death.

Lurbinectedin inhibited human monocyte activity in vitro and reduced macrophage infiltration in implanted tumors in mice.

12.2 Pharmacodynamics

Lurbinectedin exposure-response relationships and the pharmacodynamic time-course for efficacy have not been fully characterized.

Increased incidence of Grade 4 neutropenia and Grade ≥ 3 thrombocytopenia were observed with increased lurbinectedin exposure.

Cardiac Electrophysiology

No large mean increase in QTc (i.e., > 20 ms) was detected at the recommended dose of 3.2 mg/m^2.

12.3 Pharmacokinetics

Following the approved recommended dosage, geometric mean (%CV) of plasma Cmax and AUC0-inf, were 107 µg/L (79%) and 551 µg•h/L (94%), respectively. No accumulation of lurbinectedin in plasma is observed upon administrations every 3 weeks.

Distribution

The volume of distribution of lurbinectedin at steady state is 504 L (39%). Plasma protein binding is approximately 99%, to both albumin and α-1-acid glycoprotein.

Elimination

The terminal half-life of lurbinectedin is 51 hours. Total plasma clearance of lurbinectedin is 11 L/h (50%).

Metabolism

Lurbinectedin is metabolized by CYP3A in vitro.

Excretion

After a single dose of radiolabeled lurbinectedin, 89% of the radioactivity was recovered in feces (< 0.2% unchanged) and 6% in urine (1% unchanged).

Specific Populations

No clinically significant differences in the pharmacokinetics of lurbinectedin were identified based on age (18-85 years), sex, body weight (39-154 kg), or mild to moderate renal impairment (CLcr 30 to 89 mL/min). The effects of severe renal impairment (CLcr < 30 mL/min) on the pharmacokinetics of lurbinectedin have not been studied.

Hepatic Impairment

No clinically significant differences in the pharmacokinetics of lurbinectedin were identified for patients with mild hepatic impairment (total bilirubin ≤ ULN and AST > ULN or total bilirubin 1 to 1.5 × ULN and any AST) compared to that of patients with normal hepatic function.

No clinically significant differences in the pharmacokinetics of lurbinectedin were identified for patients with moderate hepatic impairment (total bilirubin > 1.5 to 3 × ULN and any AST) who received a lurbinectedin dose of 1.6 mg/m^2 compared to that of patients with mild hepatic impairment who received a dose of 3.2 mg/m^2.

No clinically significant differences in the pharmacokinetics of lurbinectedin were identified for patients with severe hepatic impairment (total bilirubin > 3 × ULN) who received a lurbinectedin dose of 1.6 mg/m^2 compared to that of patients with mild hepatic impairment who received a dose of 3.2 mg/m^2.

Drug Interactions Studies

Clinical Studies and Model-Informed Approaches

Effects of CYP3A Inhibitors on Lurbinectedin

Strong CYP3A inhibitors: Coadministration of itraconazole (200 mg once daily) increased the systemic exposure (AUC) of total lurbinectedin by 2.7-fold and unbound lurbinectedin by 2.4‑fold.

Moderate CYP3A inhibitors: Coadministration of verapamil (80 mg every 8 hours) and erythromycin (500 mg every 6 hours) is predicted to increase lurbinectedin AUC by 2.3-fold and 2.1-fold, respectively.

Weak CYP3A inhibitors: Coadministration of fluvoxamine (150 mg every 12 hours) is predicted to increase lurbinectedin AUC by 1.3-fold.

Effects of CYP3A Inducers on Lurbinectedin

Coadministration of bosentan (a moderate CYP3A inducer) decreased systemic exposure (AUC) of total lurbinectedin by 20% and unbound lurbinectedin by 19%. These changes are not considered clinically relevant.

In vitro Studies

Cytochrome P450 (CYP) Enzymes: Lurbinectedin is not an inhibitor of CYP1A2, CYP2B6, CYP2C8, CYP2C9, CYP2C19, CYP2D6, CYP2E1, or CYP3A4.

Lurbinectedin is not an inducer of CYP1A2 or CYP3A4.

Transporter Systems: Lurbinectedin is a substrate of MDR1, but is not a substrate of OATB1P1, OATP1B3, OCT1, or MATE1.

Lurbinectedin inhibits MDR1, OATP1B1, OATP1B3, and OCT1 but not BCRP, BSEP, MATE1, OAT1, OAT3, or OCT2.

13 NONCLINICAL TOXICOLOGY

13.1 Carcinogenesis, Mutagenesis, Impairment of Fertility

Carcinogenicity testing of lurbinectedin has not been performed. Lurbinectedin is genotoxic to mammalian cells in the presence and absence of metabolic activation. Lurbinectedin was not mutagenic in vitro in a bacterial reverse mutation (Ames) assay.

Fertility studies with lurbinectedin were not performed. There were no findings in reproductive organs in general toxicology studies in rats, dogs, or monkeys; however, the highest doses and exposures in these studies were all at levels lower than those at the human dose of 3.2 mg/m^2.

14 CLINICAL STUDIES

14.1 Extensive-Stage Small Cell Lung Cancer

The efficacy of ZEPZELCA in combination with intravenous (IV) atezolizumab was evaluated in IMforte (NCT05091567), a randomized, multicenter, open-label study in patients with first-line extensive-stage small cell lung cancer (ES-SCLC). Patients were eligible if their disease had not progressed after completion of four cycles of atezolizumab, carboplatin and etoposide (induction treatment) and their Eastern Cooperative Oncology Group (ECOG) performance status was 0 or 1. The trial excluded patients with CNS metastases, history of autoimmune disease, or administration of systemic immunosuppressive medications within 1 week prior to enrollment. Unless contraindicated, primary prophylaxis with granulocyte colony-stimulating factor (G-CSF) was mandated for patients assigned to the ZEPZELCA with atezolizumab arm.

The trial randomized 483 patients who had not experienced disease progression following the completion of 4 cycles of intravenous atezolizumab with carboplatin and etoposide 1:1 to one of the following treatment arms:

- ZEPZELCA 3.2 mg/m^2 IV with atezolizumab 1200 mg IV once every 3 weeks until disease progression or unacceptable toxicity, or
- Atezolizumab 1200 mg IV once every 3 weeks until disease progression or unacceptable toxicity

Randomization was stratified by ECOG performance status prior to randomization (0 vs. 1), lactate dehydrogenase (LDH) (≤ ULN vs. > ULN) prior to randomization, presence of liver metastases prior to initial study enrollment (yes vs. no), and prior receipt of prophylactic cranial irradiation (yes vs. no).

The major efficacy outcome measures were overall survival (OS) and progression-free survival (PFS) by Independent Review Facility (IRF) per RECIST v1.1.

A total of 483 patients were randomized, including 242 to the ZEPZELCA with atezolizumab arm and 241 to the atezolizumab arm. The median age was 66 years (range 35 to 85); 63% male; 82% White, 13% Asian, 0.8% were Black or African American; 7% were of Hispanic or Latino ethnicity; and 98% were current or previous smokers. Baseline ECOG performance status was 0 (43%) or 1 (57%).

Efficacy results are presented in Table 7 and Figures 1 and 2.

Table 7: Efficacy Results from IMforte
 | ZEPZELCA with Atezolizumab N=242 | Atezolizumab N=241
Overall Survival^1
Deaths (%) | 113 (47%) | 136 (56%)
Median, months | 13.2 | 10.6
(95% CI) | (11.9, 16.4) | (9.5, 12.2)
Hazard ratio^2 (95% CI) | 0.73 (0.57, 0.95)
p-value^(3, 6) | 0.0174
Progression-Free Survival^1,4,5
Number of events (%) | 174 (72%) | 202 (84%)
Median, months | 5.4 | 2.1
(95% CI) | (4.2, 5.8) | (1.6, 2.7)
Hazard ratio^2 (95% CI) | 0.54 (0.43, 0.67)
p-value^(3, 7) | < 0.0001
^1Measured from the time of randomization
^2Stratified by ECOG performance status, LDH level, presence of liver metastases and prior receipt of prophylactic cranial irradiation
^3Based on the two-sided stratified log-rank test
^4As determined by IRF
^5per RECIST v1.1 (Response Evaluation Criteria in Solid Tumors v1.1)
^6Compared to the allocated alpha of 0.0313 (two-sided) for this interim OS analysis.
^7Compared to the allocated alpha of 0.001 (two- sided) for this final PFS analysis.
CI=confidence interval

Figure 1: Progression Free survival Curve in IMforte
Figure 2: Kaplan-Meier Plot of Overall Survival in IMforte

14.2 Metastatic Small Cell Lung Cancer

PM1183-B-005-14 (Study B-005; NCT02454972) is a multicenter, open-label, multi-cohort trial evaluating ZEPZELCA as a single agent in patients with advanced or metastatic solid tumors. A cohort of patients with small cell lung cancer (SCLC) with disease progression on or after platinum-based chemotherapy received ZEPZELCA 3.2 mg/m^2 by intravenous infusion every 21 days (one cycle). Patients received a median of 4 cycles of ZEPZELCA (range 1 to 24 cycles). The trial excluded patients with central nervous system (CNS) involvement, grade ≥ 3 dyspnea, daily intermittent oxygen requirement, hepatitis or cirrhosis, and immunocompromised patients. Tumor assessments were conducted every 6 weeks for the first 18 weeks and every 9 weeks thereafter. The major efficacy outcome measure was confirmed investigator-assessed overall response rate (ORR). Additional efficacy outcome measures included duration of response (DoR), and an Independent Review Committee (IRC) assessed ORR using Response Evaluation Criteria in Solid Tumors (RECIST v1.1).

A total of 105 patients with SCLC who progressed on or after platinum-based chemotherapy were enrolled. The median age was 60 years (range: 40 to 83) with 65% of patients < 65 years and 35% of patients ≥ 65 years, and 60% were male. The majority (75%) of the patients were White, 1% were Asian, 1% were Black and 23% were not reported. Baseline ECOG performance status was 0 or 1 in 92% of patients, and 92% were former/current smokers. All patients received at least one line of platinum-based chemotherapy (range 1-2 lines), and prior radiotherapy had been administered to 71% of patients. Eight patients (8%) had prior immunotherapy in addition to platinum-based chemotherapy. Sixty patients (57%) had platinum-sensitive SCLC, defined as recurrence or progression ≥ 90 days after the last dose of platinum-containing therapy (chemotherapy free interval [CTFI] ≥ 90 days). The remaining 45 patients had platinum-resistant SCLC, defined as recurrence or progression < 90 days after the last dose of platinum-containing therapy (CTFI < 90 days).

Table 8 summarizes investigator-assessed and independent review committee assessed key efficacy measures in all patients and in platinum-resistant and platinum-sensitive subgroups.

Table 8: Efficacy Results in SCLC Cohort of Study B-005
Investigator Assessed Responsea | ZEPZELCA All Patients (n=105) | ZEPZELCA CTFI < 90 days (n=45) | ZEPZELCA CTFI ≥ 90 days (n=60)
Overall Response Rate (95% CI) | 35% (26%, 45%) | 22% (11%, 37%) | 45% (32%, 58%)
Complete response | 0% | 0% | 0%
Partial response | 35% | 22% | 45%
Duration of Response
Median in months (95% CI) | 5.3 (4.1, 6.4) | 4.7 (2.6, 5.6) | 6.2 (3.5, 7.3)
% with ≥ 6 monthsb | 35% | 10% | 44%
Independent Review Committee Assessed Responsea | All Patients (n=105) | CTFI < 90 days (n=45) | CTFI ≥ 90 days (n=60)
Overall Response Rate (95% CI) | 30% (22%, 40%) | 13% (5%, 27%) | 43% (31%, 57%)
Complete response | 0% | 0% | 0%
Partial response | 30% | 13% | 43%
Duration of Response
Median in months (95% CI) | 5.1 (4.9, 6.4) | 4.8 (2.4, 5.3) | 5.3 (4.9, 7.0)
% with ≥ 6 monthsb | 25% | 0% | 31%
CI: confidence interval, CTFI: chemotherapy free interval.
a Confirmed overall response rate.
b Based on observed duration of response.

15 REFERENCES

1. "OSHA Hazardous Drugs." OSHA. http://www.osha.gov/SLTC/hazardousdrugs/index.html

16 HOW SUPPLIED/STORAGE AND HANDLING

How Supplied

ZEPZELCA (lurbinectedin) for injection is supplied as a sterile, preservative-free, white to off-white lyophilized powder in a single-dose clear glass vial. Each carton (NDC 68727-712-01) contains 4 mg in one single-dose vial.

Storage and Handling

Store refrigerated at 2°C to 8°C (36°F to 46°F).

ZEPZELCA is a hazardous drug. Follow applicable special handling and disposal procedures^1.

17 PATIENT COUNSELING INFORMATION

Advise the patient to read the FDA-approved patient labeling (Patient Information).

Myelosuppression

Advise patients that ZEPZELCA can cause myelosuppression. Inform patients about the signs and symptoms of myelosuppression and to immediately contact their healthcare provider if signs or symptoms occur [see Warnings and Precautions (5.1)].

Hepatotoxicity

Advise patients that ZEPZELCA can cause hepatotoxicity and to contact their healthcare provider immediately if signs or symptoms occur [see Warnings and Precautions (5.2)].

Extravasation Resulting in Tissue Necrosis

Advise patients that administration of ZEPZELCA through a central venous catheter is recommended because extravasation of ZEPZELCA can cause skin and soft tissue injury, including necrosis requiring debridement. Advise patients to contact their healthcare provider immediately for signs or symptoms of extravasation. The time to onset of necrosis after extravasation may vary [see Warnings and Precautions (5.3)].

Rhabdomyolysis

Advise patients that rhabdomyolysis has been reported with the use of ZEPZELCA and to contact their healthcare provider immediately for signs and symptoms of rhabdomyolysis [see Warnings and Precautions (5.4)].

Embryo-Fetal Toxicity

- Advise pregnant women and females of reproductive potential of the potential risk to a fetus. Advise females to inform their healthcare provider of a known or suspected pregnancy [see Warnings and Precautions (5.5), Use in Specific Populations (8.1)].
- Advise females of reproductive potential to use effective contraception during treatment with ZEPZELCA and for 6 months after the last dose [see Use in Specific Populations (8.3)].
- Advise males with female partners of reproductive potential to use effective contraception during treatment with ZEPZELCA and for 4 months after the last dose [see Use in Specific Populations (8.3)].

Lactation

Advise women not to breastfeed during treatment with ZEPZELCA and for at least 2 weeks after the last dose [see Use in Specific Populations (8.2)].

Drug Interactions

Advise patients to inform their healthcare providers of all concomitant medications, herbal and dietary supplements. Advise patients to avoid grapefruit products and Seville oranges during treatment with ZEPZELCA [see Drug Interactions (7.1)].

Distributed by:
Jazz Pharmaceuticals, Inc.
Palo Alto, CA 94306

Under license from Pharma Mar, S.A.

Protected by U.S. Patent No. 7,763,615

Patient Package Insert

PATIENT INFORMATION

ZEPZELCA® (zep zel' kah)

(lurbinectedin)

for injection

What is ZEPZELCA?

ZEPZELCA may be used to treat adults with a kind of lung cancer called small cell lung cancer (SCLC):

- ZEPZELCA may be used in combination with atezolizumab or atezolizumab and hyaluronidase-tqjs as maintenance treatment when your lung cancer:
  - is a type called “extensive-stage”, which means it has spread or grown, and
  - has not progressed after first treatment with atezolizumab or atezolizumab and hyaluronidase-tqjs and the chemotherapy medicines carboplatin and etoposide.
- ZEPZELCA may be used when your lung cancer:
  - has spread to other parts of the body (metastatic), and
  - you have received treatment with chemotherapy that contains platinum, and it did not work or is no longer working.

It is not known if ZEPZELCA is safe and effective in children.

Before receiving ZEPZELCA, tell your healthcare provider about all of your medical conditions, including if you:

- have liver or kidney problems.
- are pregnant or plan to become pregnant. ZEPZELCA can harm your unborn baby.
  Females who are able to become pregnant:
  - Your healthcare provider should do a pregnancy test before you start treatment with ZEPZELCA.
  - You should use effective birth control (contraception) during treatment with and for 6 months after your last dose of ZEPZELCA.
  - Tell your healthcare provider right away if you become pregnant or think that you are pregnant during treatment with ZEPZELCA.
Males with female partners who are able to become pregnant should use effective birth control during treatment with and for 4 months after your last dose of ZEPZELCA.
- are breastfeeding or plan to breastfeed. It is not known if ZEPZELCA passes into your breastmilk. Do not breastfeed during treatment with ZEPZELCA and for 2 weeks after your last dose of ZEPZELCA. Talk to your healthcare provider about the best way to feed your baby during treatment with ZEPZELCA.

Tell your healthcare provider about all the medicines you take, including prescription and over-the-counter medicines, vitamins, and herbal supplements. Certain other medicines may affect how ZEPZELCA works. Know the medicines you take. Keep a list of them to show your healthcare provider and pharmacist when you get a new medicine.

How will I receive ZEPZELCA?

- ZEPZELCA is given by an intravenous (IV) infusion into a vein over 60 minutes.
- ZEPZELCA is usually given every 21 days.
- Before each treatment with ZEPZELCA, you may receive medicines to help prevent nausea and vomiting or make it less severe.
- Your healthcare provider will decide how long you will continue treatment with ZEPZELCA.
- Your healthcare provider may do certain tests during your treatment with ZEPZELCA to check you for side effects, and to see how well you respond to the treatment.

What should I avoid while using ZEPZELCA?

- Avoid eating or drinking grapefruit, Seville oranges, or products that contain grapefruit juice and Seville oranges during treatment with ZEPZELCA.

What are the possible side effects of ZEPZELCA?

ZEPZELCA can cause serious side effects, including:

- Low blood cell counts. Low blood counts including low neutrophil counts (neutropenia) and low platelet counts (thrombocytopenia) are common with ZEPZELCA, and can also be severe. Some people with low white blood cell counts may get fever, or an infection throughout the body (sepsis), that can cause death. Your healthcare provider should do blood tests before you receive each treatment with ZEPZELCA to check your blood cell counts.
  Tell your healthcare provider right away if you develop:
  - fever or any other signs of infection
  - unusual bruising or bleeding
  - tiredness
  - pale colored skin
- Liver problems. Increased liver function tests are common with ZEPZELCA and can also be severe. Your healthcare provider should do blood tests to check your liver function before you start and during treatment with ZEPZELCA.
  Tell your healthcare provider right away if you develop symptoms of liver problems including:
  - loss of appetite
  - nausea or vomiting
  - pain on the right side of your stomach-area (abdomen)
- Skin damage at or near the infusion site. ZEPZELCA can cause damage and death of tissue cells if it leaks into the tissues around your infusion site. You may need to have surgery to remove any dead tissue. Tell your healthcare provider right away if you see any fluid leaking at or around the catheter during your infusion, or if you notice any redness, swelling, itching or discomfort at the infusion site at any time.
- Severe muscle problems (rhabdomyolysis). Treatment with ZEPZELCA may increase the level of an enzyme in your blood called creatine phosphokinase (CPK). Your healthcare provider should do blood tests to check your CPK levels before you start and during treatment with ZEPZELCA. Tell your healthcare provider if you have severe muscle pain or weakness.

Your healthcare provider may temporarily stop treatment, lower your dose, or permanently stop ZEPZELCA if you develop serious side effects during treatment with ZEPZELCA.

The most common side effects of ZEPZELCA given alone include:

- tiredness
- low white and red blood cell counts
- increased kidney function blood test (creatinine)
- increased liver function blood tests
- increased blood sugar (glucose)
- nausea
- decreased appetite
- muscle and joint (musculoskeletal) pain
- low level of albumin in the blood
- constipation
- trouble breathing
- low levels of sodium and magnesium in the blood
- vomiting
- cough
- diarrhea

The most common side effects of ZEPZELCA given with atezolizumab include:

- low white and red blood cell counts
- nausea
- tiredness or weakness

These are not all of the possible side effects of ZEPZELCA. Call your doctor for medical advice about side effects. You may report side effects to FDA at 1‑800‑FDA‑1088.

General information about the safe and effective use of ZEPZELCA.

Medicines are sometimes prescribed for purposes other than those listed in a Patient Information leaflet. If you would like more information, talk with your healthcare provider. You can ask your pharmacist or healthcare provider for information about ZEPZELCA that is written for health professionals.

What are the ingredients in ZEPZELCA?
Active ingredient: lurbinectedin
Inactive ingredients: sucrose, lactic acid and sodium hydroxide.

Distributed by: Jazz Pharmaceuticals, Inc.

Palo Alto, CA 94306

Under license from Pharma Mar, S.A.

ZEPZELCA is a registered trademark of Pharma Mar, S.A.

For more information, go to www.ZEPZELCA.com or call 1-800-520-5568.

This Patient Information has been approved by the U.S. Food and Drug Administration. Revised:10/2025

PACKAGE/LABEL PRINCIPAL DISPLAY PANEL

Carton:

NDC 68727-712-01
ZEPZELCA
(lurbinectedin)
for injection
4 mg per vial
FOR INTRAVENOUS INFUSION ONLY
Reconstitute before further dilution.
Each single-dose vial contains 4 mg of lurbinectedin
as a sterile lyophilized powder
Rx Only
Single-dose vial
Discard unused portion.
Caution: Cytotoxic agent

Package/Label Display Panel

Vial:

NDC 68727-712-01
ZEPZELCA
(lurbinectedin)
for injection
4 mg per vial
FOR INTRAVENOUS INFUSION ONLY
Single-Dose Vial.
Discard unused portion.